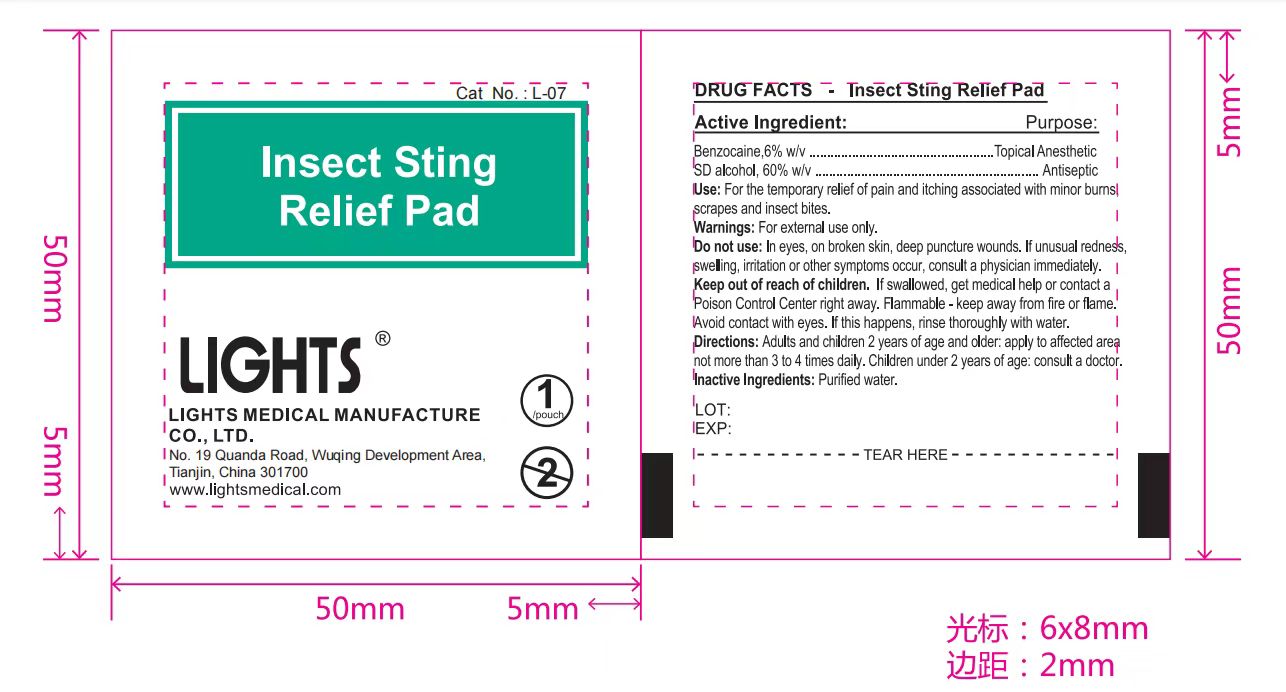 DRUG LABEL: LIGHTS Insect Sting Relief Pad
NDC: 61333-213 | Form: SOLUTION
Manufacturer: Lights Medical Manufacture Co., Ltd.
Category: otc | Type: HUMAN OTC DRUG LABEL
Date: 20260121

ACTIVE INGREDIENTS: BENZOCAINE 6 g/100 g; ALCOHOL 60 g/100 g
INACTIVE INGREDIENTS: WATER

61333-213 Sting Relief

Active Ingredient

Benzocaine 6% w/v

SD Alcohol: 60% w/v

Purpose

Topical Anesthetic

Antiseptic

INDICATIONS AND USAGE

Uses: For temporary relief of pain and itching associated with minor burns, scrapes, and insect bites

Warnings:

For external use only

Do not use: In the eyes, on broken skin, deep puncture wounds. If unusal redness, swelling, irritation, or other symptoms occur, consult a physician immediately.

Keep out of reach of children. If swallowed, get medical help or contact a Poison Control Center right away

Flammable. Keep away from fire or flame. Avoid contact with eyes. If this happens, rinse thoroughly with water.

Directions

Adults and children 2 yeas of Age or older: Apply to affected area no more than 3-4 times daily

Children under 2 yeas of Age or older: Consult a doctor

Inactive Ingredient

Purified Water